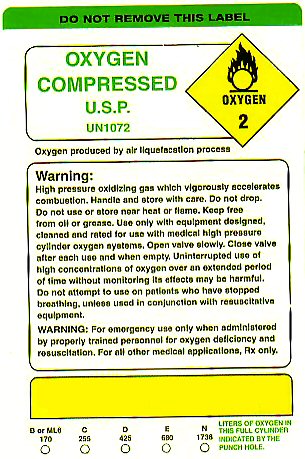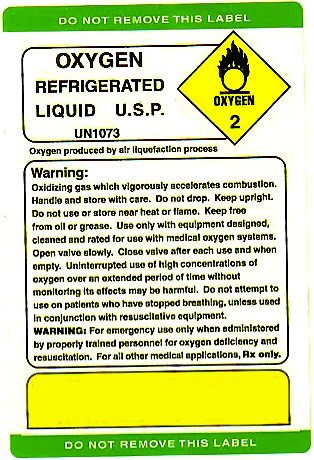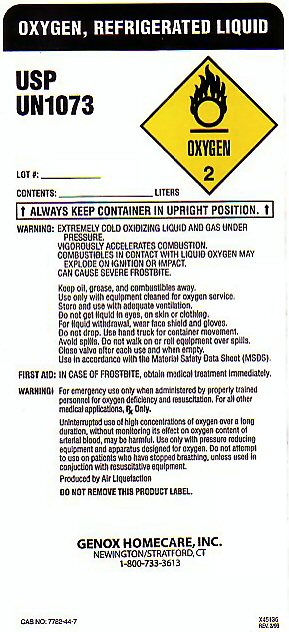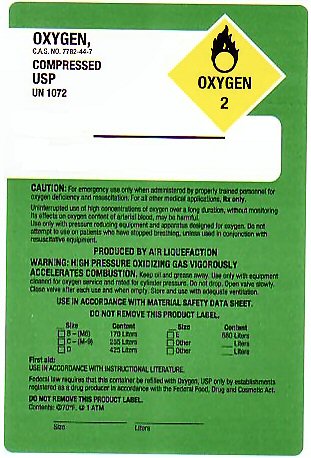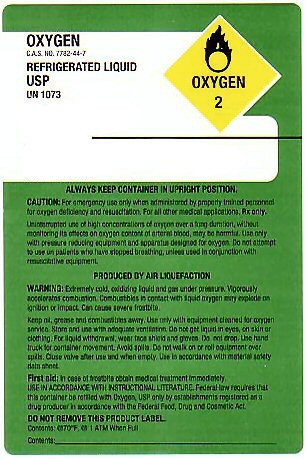 DRUG LABEL: OXYGEN
NDC: 63289-001 | Form: GAS
Manufacturer: Landauer Metropolitan, Inc
Category: prescription | Type: HUMAN PRESCRIPTION DRUG LABEL
Date: 20100101

ACTIVE INGREDIENTS: OXYGEN 99 L/100 L

OXYGEN COMPRESSED LABEL

OXYGEN COMPRESSED USP CAS NO 7782-44-7 UN 1072 OXYGEN-2

PRODUCED BY AIR LIQUEFACTION. USE IN ACCORDANCE WITH MATERIAL SAFETY DATA SHEET DO NOT REMOVE THIS PRODUCT LABEL

SIZE CONTENT

M6 170 LITERS

ML6 170 LITERS

D 425 LITERS

E 680 LITERS

N 1736

OXYGEN REFRIGERATED LIQUID USP CAS NO 7782-44-7 UN 1073 OXYGEN-2

ALWAYS KEEP CONTAINER IN UPRIGHT POSITION. DO NOT REMOVE THIS PRODUCT LABEL CONTENTS AT 70 F AND 1 ATM WHEN FULL CONTENTS___________________________

FIRST AID: IN CASE OF FROSTBITE OBTAIN MEDICAL TREATMENT IMMEDIATELY. USE IN ACCORDANCE WITH INSTRUCTIONAL LITERATURE. FEDERAL LAW REQUIRES THAT THIS CONTAINER BE REFILLED WITH OXYGEN USP ONLY BY ESTABLISHMENTS REGISTERED AS A DRUG PRODUCER IN ACCORDANCE WITH THE FEDERAL FOOD DRUG AND COSMETIC ACT.

PRODUCT WARNINGS AND PRECAUTIONS

WARNING: FOR EMERGENCY USE ONLY WHEN ADMINISTERED BY PROPERLY TRAINED PERSONNEL FOR OXYGEN DEFICIENCY AND RESUSCITATION. FOR ALL OTHER MEDICAL APPLICATIONS Rx ONLY.

WARNING: HIGH PRESSURE OXIDIZING GAS WHICH VIGOROUSLY ACCELERATES COMBUSTION. HANDLE AND STORE WITH CARE. DO NOT DROP. DO NOT USE OR STORE NEAR HEAT OR FLAME. KEEP FREE FROM OIL AND GREASE. USE ONLY WITH EQUIPMENT DESIGNED, CLEANED, AND RATED FOR USE WITH MEDICAL HIGH PRESSURE CYLINDER OXYGEN SYSTEMS. OPEN VALVE SLOWLY. CLOSE VALVE AFTER EACH USE AND WHEN EMPTY. UNINTERRUPTED USE OF HIGH CONCENTRATIONS OF OXYGEN OVER AN EXTENDED PERIOD OF TIME WITHOUT MONITORING ITS EFFECTS MAY BE HARMFUL. DO NOT ATTEMPT TO USE ON PATIENTS WHO HAVE STOPPED BREATHING, UNLESS USED IN CONJUNCTION WITH RESUSCITATIVE EQUIPMENT.

LIQUID PRODUCT WARNINGS AND PRECAUTIONS

WARNING: EXTREMELY COLD OXIDIZING LIQUID AND GAS UNDER PRESSURE. VIGOROUSLY ACCELERATES COMBUSTION. COMBUSTIBLES IN CONTACT WITH LIQUID OXYGEN MAY EXPLODE ON IGNITION OR IMPACT. CAN CAUSE SEVERE FROSTBITE.

DO NOT GET LIQUID IN EYES, ON SKIN, OR CLOTHING. FOR LIQUID WITHDRAWAL WEAR FACE SHIELD AND GLOVES. AVOID SPILLS. DO NOT WALK ON OR ROLL EQUIPMENT OVER SPILLS. CLOSE VALVE AFTER EACH USE AND WHEN EMPTY. USE IN ACCORDANCE WITH THE MATERIAL SAFETY DATA SHEET (MSDS).

FIRST AID: IN CASE OF FROSTBITE OBTAIN MEDICAL TREATMENT IMMEDIATELY.